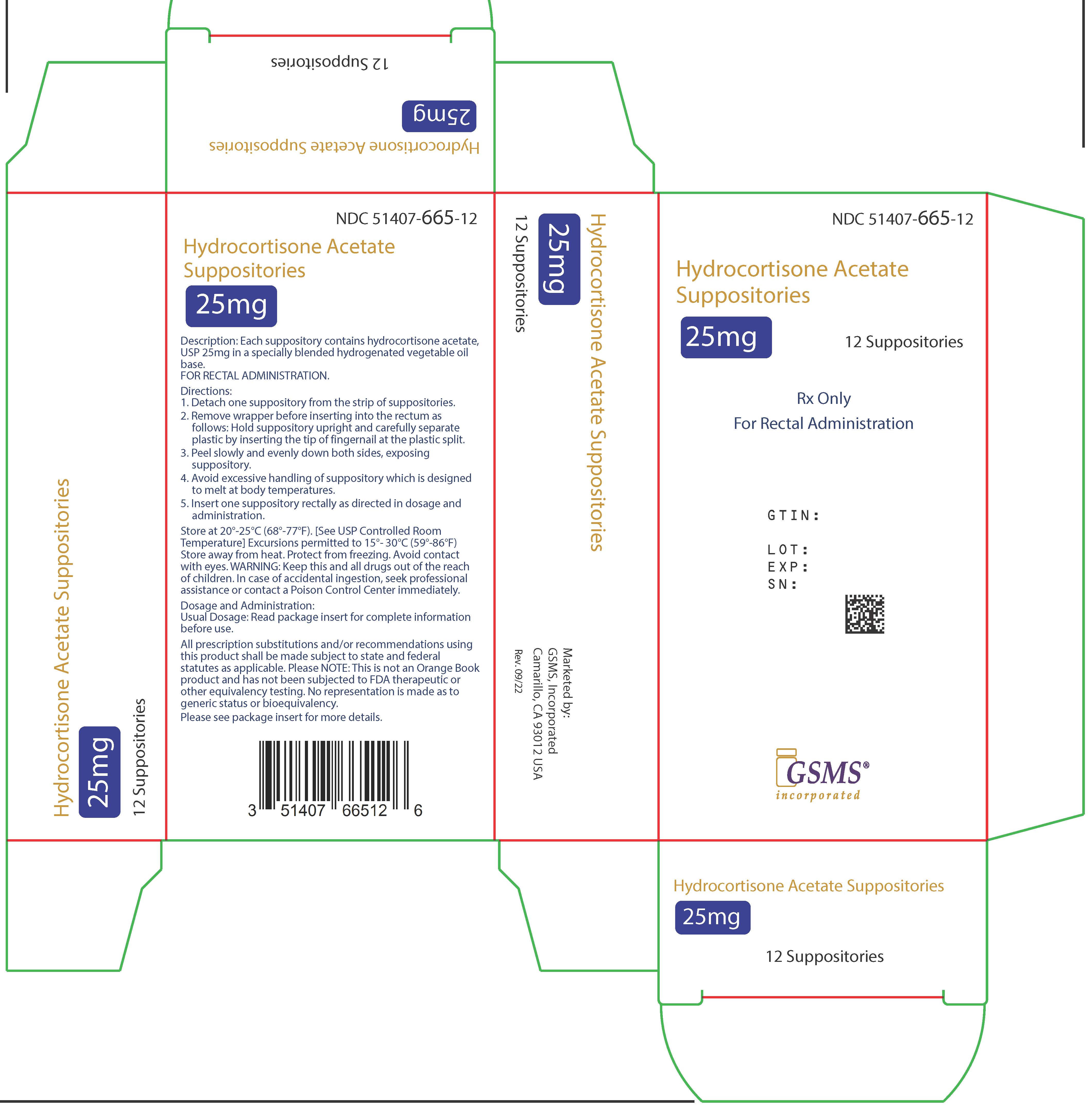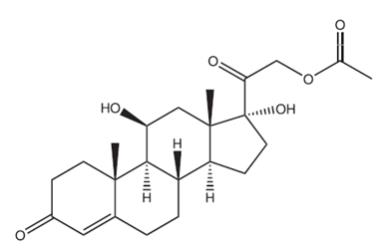 DRUG LABEL: HYDROCORTISONE ACETATE
NDC: 51407-665 | Form: SUPPOSITORY
Manufacturer: Golden State Medical Supply, Inc.
Category: prescription | Type: HUMAN PRESCRIPTION DRUG LABEL
Date: 20250224

ACTIVE INGREDIENTS: HYDROCORTISONE ACETATE 25 mg/1 1
INACTIVE INGREDIENTS: HYDROGENATED PALM KERNEL OIL

Hydrocortisone Acetate

Hydrocortisone Acetate Suppositories 25mg

Rx Only
For Rectal Administration

DESCRIPTION:

Hydrocortisone acetate is a corticosteroid designed chemically as pregn-4-ene 3, 20-dione, 21-(acetyloxy)-11, 17-dihydroxy––(11 β) with the following structural formula:

Each rectal suppository contains hydrocortisone acetate, USP 25 mg in a specially blended hydrogenated vegetable oil base.

CLINICAL PHARMACOLOGY:

In normal subjects, about 26% of hydrocortisone acetate is absorbed when the suppository is applied to the rectum. Absorption of hydrocortisone acetate may vary across abraded or inflamed surfaces. Topical steroids are primarily effective because of their anti-inflammatory, anti-pruritic and vasoconstrictive action.

INDICATIONS AND USAGE:

Hydrocortisone Acetate suppositories are indicated for use in inflamed hemorrhoids, post-irradiation (factitial) proctitis; as an adjunct in the treatment of chronic ulcerative colitis; cryptitis; and other inflammatory conditions of anorectum and pruritus ani.

CONTRAINDICATIONS:

Hydrocortisone Acetate suppositories are contraindicated in those patients having a history of hypersensitivity to hydrocortisone acetate or any of the components.

PRECAUTIONS:

Do not use Hydrocortisone Acetate suppositories unless adequate proctologic examination is made. If irritation develops, the product should be discontinued and appropriate therapy instituted. In the presence of an infection, the use of an appropriate antifungal or antibacterial agent should be instituted. If a favorable response does not occur promptly, Hydrocortisone Acetate should be discontinued until the infection has been adequately controlled.

Carcinogenesis:

No long term studies in animals have been performed to evaluate the carcinogenic potential of corticosteroid suppositories.

Pregnancy Category C:

In laboratory animals, topical steroids have been associated with an increase in the incidence of fetal abnormalities when gestating females have been exposed to rather low dosage levels. There are no adequate and well controlled studies in pregnant women. Hydrocortisone Acetate suppositories should only be used during pregnancy if the potential benefit justifies the risk to the fetus. Drugs of this class should not be used extensively on pregnant patients, in large amounts, or for prolonged periods of time.

It is not known whether this drug is excreted in human milk and because many drugs are excreted in human milk and because of the potential for serious adverse reactions in nursing infants from Hydrocortisone Acetate suppositories, a decision should be

made whether to discontinue nursing or to discontinue the drug, taking into account the importance of the drug to the mother.

ADVERSE REACTIONS:

The following local adverse reactions have been reported with corticosteroid suppositories; burning, itching, irritation, dryness, folliculitis, hypopigmentation, allergic contact dermatitis, secondary infection.

Drug abuse and dependence have not been reported in patients treated with Hydrocortisone Acetate suppositories.

OVERDOSAGE:

If signs and symptoms of systemic overdosage occur, discontinue use.

DOSAGE AND ADMINISTRATION:

For rectal administration. Detach one suppository from strip of suppositories. Remove the wrapper. Avoid excessive handling of the suppository which is designed to melt at body temperature. Insert suppository into the rectum with gentle pressure, pointed end first. Insert one suppository in the rectum twice daily, morning and night for two weeks, in nonspecific proctitis. In more severe cases, one suppository three times a day or two suppositories twice daily. In factitial proctitis, the recommended duration of therapy is six to eight weeks or less, according to the response of the individual case.

All prescription substitutions and/or recommendations using this product shall be made subject to state and federal statutes as applicable. Please NOTE: This is notan Orange Book product and hasnot been subjected to FDA therapeutic or other equivalencytesting. No representation is made asto generic status orbioequivalency. Each person recommending a prescription substitution using this product shall make such recommendation based on his/her professional knowledge and opinion, upon evaluating the active ingredients, inactive ingredients, excipients and chemical information provided herein.

HOW SUPPLIED:

Hydrocortisone Acetate suppositories, 25mg are off-white, smooth surfaced and bullet shaped with one pointed end.

Box of 12 and 24 suppositories, NDC 51407-665-12 and NDC 51407-665-24.

STORAGE:

Store at 20º-25ºC (68º-77ºF) [See USP Controlled Room Temperature]. Excursions permitted to 15º-30ºC (59º-86ºF). Store away from heat. Protect from freezing.

Manufactured for:
Laser Pharmaceuticals, LLC

1015 Nine North Drive, Ste 400

Alpharetta, GA 30004
770-754-9846

Rev. 08/24

Marketed by:

GSMS, Inc.

Camarillo, CA 93012 USA